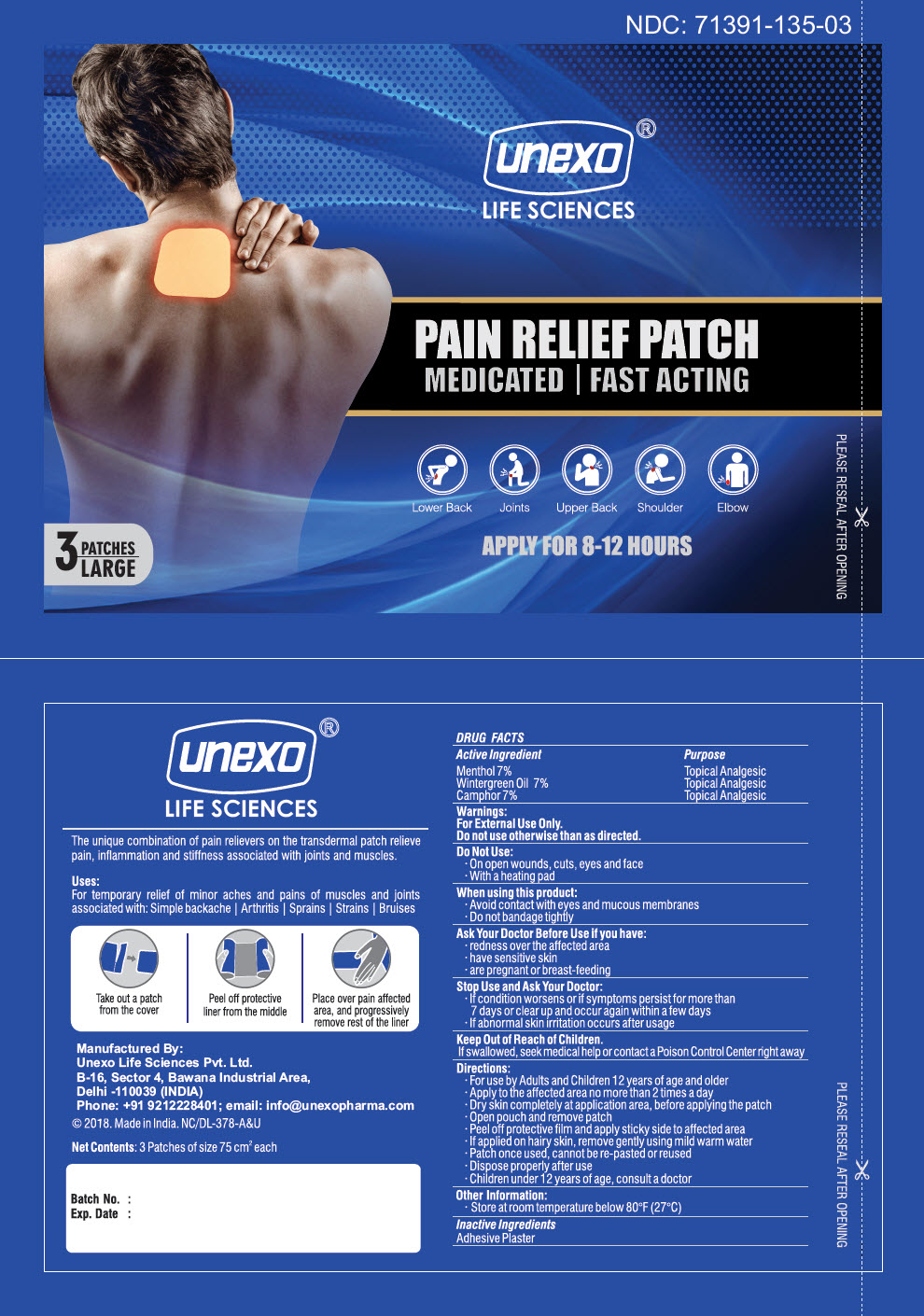 DRUG LABEL: PAIN RELIEF
NDC: 71391-135 | Form: PATCH
Manufacturer: Unexo Life Sciences, Private Limited
Category: otc | Type: HUMAN OTC DRUG LABEL
Date: 20210112

ACTIVE INGREDIENTS: MENTHOL, UNSPECIFIED FORM 78 mg/1 1; METHYL SALICYLATE 78 mg/1 1; CAMPHOR (SYNTHETIC) 78 mg/1 1

PAIN RELIEF

DRUG FACTS

ACTIVE INGREDIENT

Active Ingredient | Purpose
Menthol 7% | Topical Analgesic
Wintergreen Oil 7% | Topical Analgesic
Camphor 7% | Topical Analgesic

Uses

For temporary relief of minor aches and pains of muscles and joints associated with: Simple backache | Arthritis | Sprains | Strains | Bruises

Warnings

For External Use Only.

Do not use otherwise than as directed.

Do Not Use

- On open wounds, cuts, eyes and face
- With a heating pad

When using this product

- Avoid contact with eyes and mucous membranes
- Do not bandage tightly

Ask Your Doctor Before Use if you have

- redness over the affected area
- have sensitive skin
- are pregnant or breast-feeding

Stop Use and Ask Your Doctor

- If condition worsens or if symptoms persist for more than 7 days or clear up and occur again within a few days
- If abnormal skin irritation occurs after usage

Keep Out of Reach of Children.

If swallowed, seek medical help or contact a Poison Control Center right away

Directions

- For use by Adults and Children 12 years of age and older
- Apply to the affected area no more than 2 times a day
- Dry skin completely at application area, before applying the patch
- Open pouch and remove patch
- Peel of protective film and apply sticky side to affected area
- If applied on hairy skin, remove gently using mild warm water
- Patch once used, cannot be re-pasted or reused
- Dispose properly after use
- Children under 12 years of age, consult a doctor

Other Information

- Store at room temperature below 80°F (27°C)

Inactive Ingredients

Adhesive Plaster

Manufactured By:
Unexo Life Sciences Pvt. Ltd.
B-16, Sector 4, Bawana Industrial Area,
Delhi -110039 (INDIA)

PRINCIPAL DISPLAY PANEL - 3 Patch Pouch

NDC: 71391-135-03

unexo®
LIFE SCIENCES

PAIN RELIEF PATCH
MEDICATED | FAST ACTING

Lower Back
Joints
Upper Back
Shoulder
Elbow

APPLY FOR 8-12 HOURS

3 PATCHES
LARGE

PLEASE RESEAL AFTER OPENING